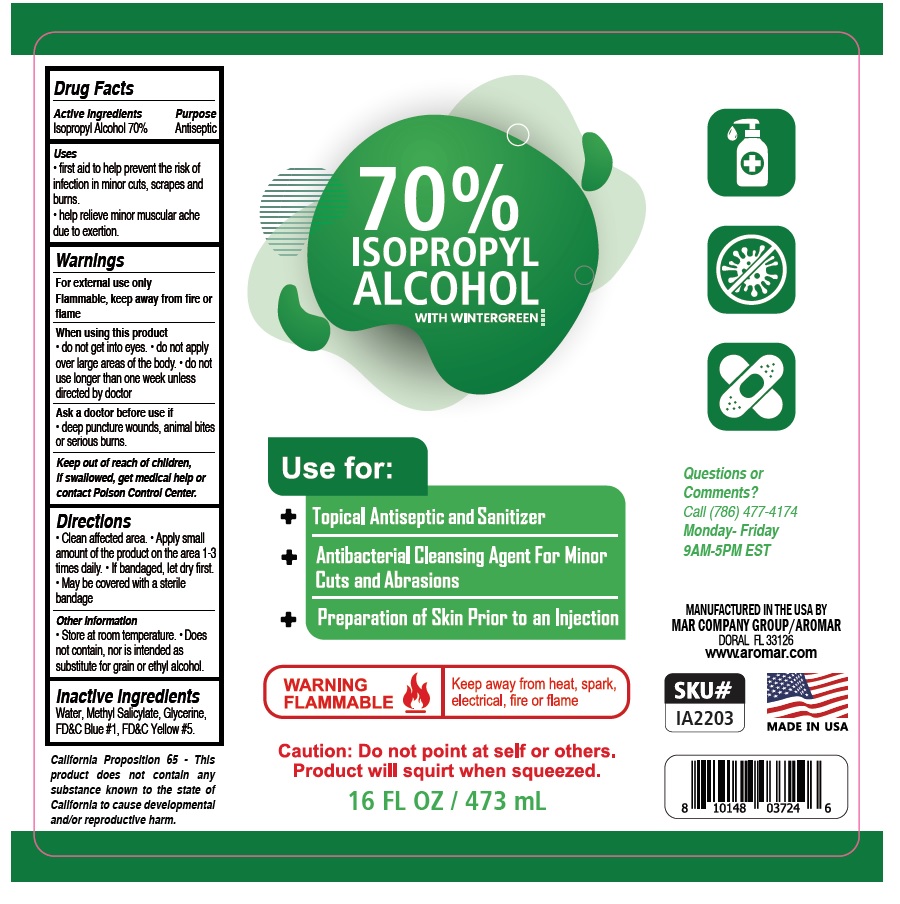 DRUG LABEL: 70% ISOPROPYL ALCOHOL WITH WINTERGREEN
NDC: 73717-606 | Form: LIQUID
Manufacturer: Mar Company Distributors, LLC
Category: otc | Type: HUMAN OTC DRUG LABEL
Date: 20210205

ACTIVE INGREDIENTS: ISOPROPYL ALCOHOL 70 mL/100 mL
INACTIVE INGREDIENTS: WATER; METHYL SALICYLATE; GLYCERIN; FD&C BLUE NO. 1; FD&C YELLOW NO. 5

70% ISOPROPYL ALCOHOL WITH WINTERGREEN

Active Ingredients

Isopropyl Alcohol 70%

Purpose

Antiseptic

Uses

• first aid to help prevent the risk of infection in minor cuts, scrapes and burns.

• help relieve minor muscular ache due to exertion.

Warnings

For external use only

Flammable, keep away from fire or flame

When using this product

• do not get into eyes. • do not apply over large areas of the body. • do not use longer than one week unless directed by doctor

Ask a doctor before use if

• deep puncture wounds, animal bites or serious burns.

Keep out of reach of children. If swallowed, get medical help or contact Poison Control Center.

Directions

• Clean affected area. • Apply small amount of the product on the area 1-3 times daily. • If bandaged, let dry first. • May be covered with a sterile bandage

Other Information

• Store at room temperature. • Does not contain, nor is intended as substitute for grain or ethyl alcohol.

Inactive Ingredients

Water, Methyl Salicylate, Glycerine, FD&C Blue #1, FD&C Yellow #5.

Use for:

+ Topical Antiseptic and Sanitizer

+ Antibacterial Cleansing Agent For Minor Cuts and Abrasions

+ Preparation of Skin Prior to an Injection

WARNING FLAMMABLE

Keep away from heat, spark, electrical, fire or flame

Caution: Do not point at self and others. Product will squirt when squeezed.

Questions or Comments?

Call (786) 477-4174

Monday- Friday 9AM-5PM EST

MANUFACTURED IN THE USA BY

MAR COMPANY GROUP/AROMAR

DORAL FL33126

www.aromar.com

MADE IN USA

California Proposition 65 - This product does not contain any substance known to the state of California to cause developmental and/or reproductive harm.